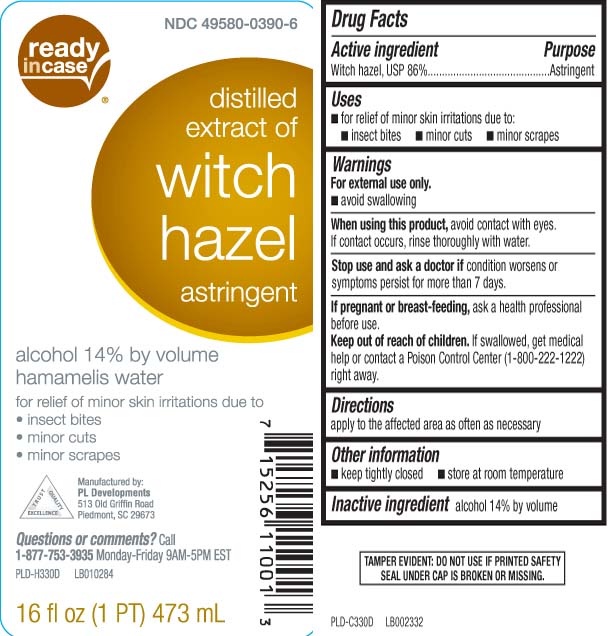 DRUG LABEL: Witch Hazel
NDC: 49580-0390 | Form: LIQUID
Manufacturer: P & L Development, LLC
Category: otc | Type: HUMAN OTC DRUG LABEL
Date: 20250212

ACTIVE INGREDIENTS: WITCH HAZEL 86 g/100 mL
INACTIVE INGREDIENTS: ALCOHOL

Drug Facts

Active ingredient

Witch hazel, USP 86%

Purpose

Astringent

Uses

- for relief of minor skin irritations due to:
  - insect bites
  - minor cuts
  - minor scrapes

Warnings

- for external use only
- avoid swallowing

When using this product

- avoid contact with the eyes. If contact occurs, rinse thoroughly with water.

Stop use and ask a doctor if

condition worsens or symptoms persist for more than 7 days.

If pregnant or breast-feeding,

ask a health professional before use.

Keep out of reach of children.

If swallowed, get medical help or contact a Poison Control Center (1-800-222-1222) right away.

Directions

apply to the affected area as often as necessary.

Other information

- keep tightly closed
- store at room temperature

Inactive ingredient

alcohol 14% by volume

Principal Display Panel

Distilled extract of

Witch Hazel

Astringent

alcohol 14% by volume

hamamelis water

for relief of minor skin irritations due to

- insect bites
- minor cuts
- minor scrapes

fl oz (PT) mL

Manufactured by:

PL Developments

513 Old Griffen Road

Piedmont, SC 29673

Questions or comments?

Call 1-877-753-3935 Monday-Friday 9AM-5PM EST

TAMPER EVIDENT: DO NOT USE IF PRINTED SAFETY SEAL UNDER CAP IS BROKEN OR MISSING.

Package Label

READYinCASE Astringent